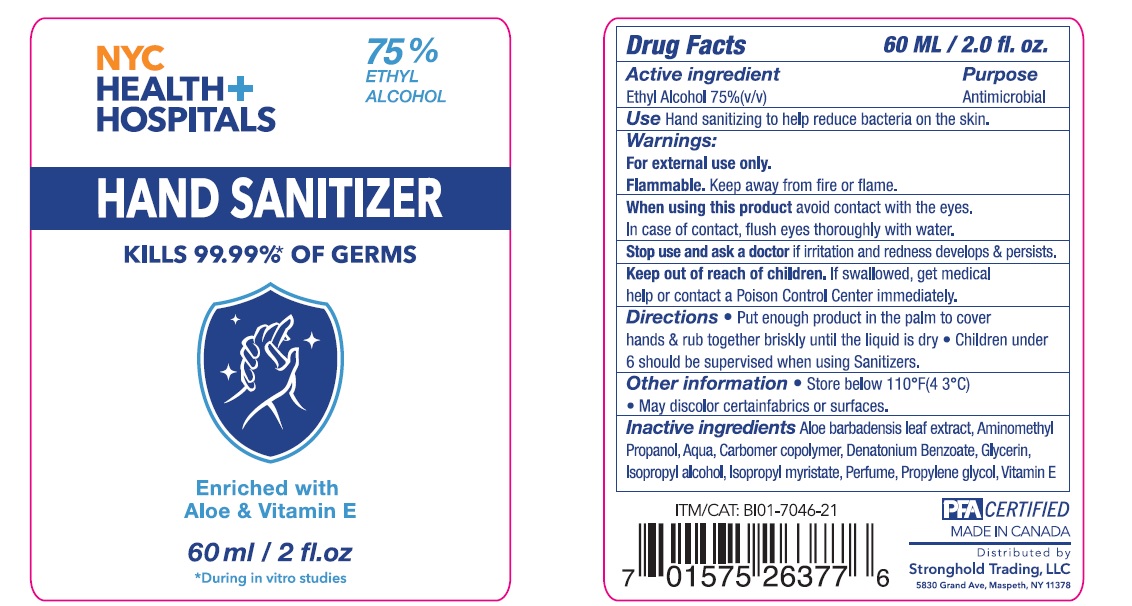 DRUG LABEL: NYC Health Hospitals
NDC: 50157-340 | Form: GEL
Manufacturer: Brands International
Category: otc | Type: HUMAN OTC DRUG LABEL
Date: 20210224

ACTIVE INGREDIENTS: ALCOHOL 0.75 mL/1 mL
INACTIVE INGREDIENTS: WATER; ISOPROPYL ALCOHOL; ALOE VERA LEAF; DENATONIUM BENZOATE; GLYCERIN; ISOPROPYL MYRISTATE; .ALPHA.-TOCOPHEROL ACETATE, D-; AMINOMETHYLPROPANOL; CARBOMER COPOLYMER TYPE A (ALLYL PENTAERYTHRITOL CROSSLINKED); PROPYLENE GLYCOL

NYC Health+ Hospitals: Hand Sanitizer

Active Ingredients

Ethyl Alcohol 75%v/v.

Purpose: Antimicrobial

Purpose

Antimicrobial

Uses

- helps reduce bacteria on the skin that could cause disease
- Recommended for repeated use

Warnings

For external use only.

Flammable. Keep away from fire or flame.

Safety Instructions

Flammable, Keep away from fire and flame

Ask Doctor

Stop Use and Ask a doctor if irritation or redness develops

KEEP OUT OF REACH OF CHILDREN

If swallowed, get medical help or contact Poison Control right away

Other Information

Store below 110°F (43°C)
May discolor certain fabrics or surfaces.

Directions

- Place enough product in your palm to thoroughly cover your hands
- Rub hands together briskly until dry
- Children under 6 years of age should be supervised when using this product.

Inactive Ingredients

water, isopropyl alcohol, glycerin, carbomer copolymer, aminomethyl propanol, fragrance, propylene glycol, isopropyl myristate, propylene glycol, Aloe, Tocopheryl Acetate. Please review Label for further details